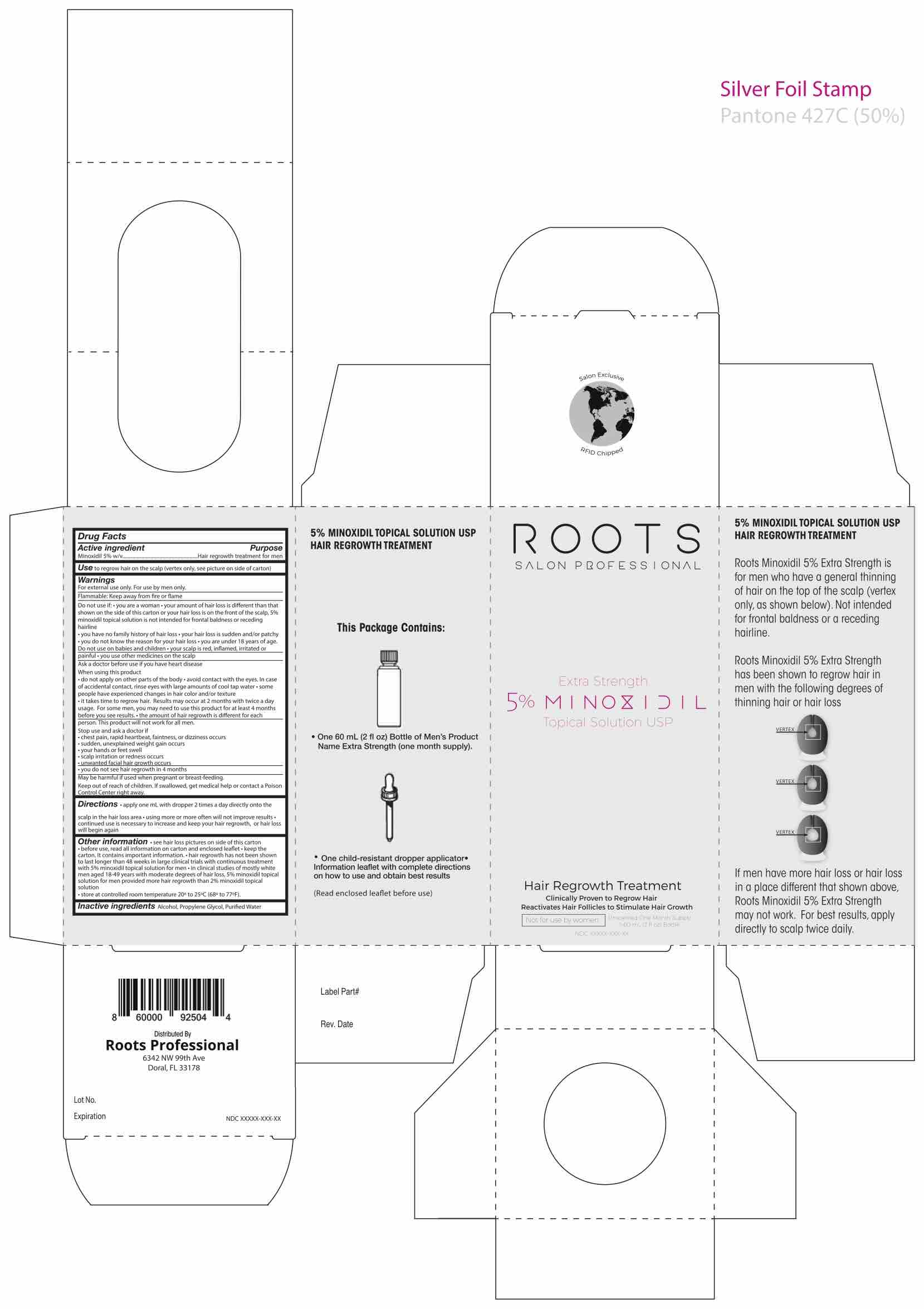 DRUG LABEL: Roots Professional - Topical Solution Hair Regrowth Treatment
NDC: 73359-002 | Form: SOLUTION
Manufacturer: Roots Hair Club, LLC
Category: otc | Type: HUMAN OTC DRUG LABEL
Date: 20230110

ACTIVE INGREDIENTS: MINOXIDIL 5 g/100 mL
INACTIVE INGREDIENTS: ISOPROPYL ALCOHOL; PROPYLENE GLYCOL; WATER

Roots Professional - 5% Minoxidil Topical Solution Hair Regrowth Treatment

ACTIVE INGREDIENT

Minoxidil 5% w/v

PURPOSE

Hair regrowth treatment for men

USE

Use to regrow hair on the top of the scalp (vertex only, see pictures on side of carton).

WARNINGS

For external use only. For use by men only.

Flammable: Keep away from fire or flame

Do not use if:

- You are a woman
- Your amount of hair loss is different than shown on the side of this carton or hair loss is on the front of the scalp, 5% minoxidil topical solution is not intended for frontal baldness or receding hairline
- You have no family history of hair loss
- Your hair loss is sudden and/or patchy
- You do not know the reason for your hair loss
- You are under 18 years of age. Do not use on babies or children
- Your scalp is red, inflamed, infected, irritated, or painful
- You use other medicines on the scalp

ASK DOCTOR

Ask your doctor before use if you have heart disease.

When using this product

- Do not apply on other parts of the body
- Avoid contact with the eyes. In case of accidental contact, rinse eyes with large amounts of cool tap water
- Some people have expereinced changes in hair color and/or texture
- It takes time to regrow hair. Results may occur at 2 months with twice a day usage. For some men, you may need to use this product for at least 4 months before you see results
- The amount of hair regrowth is different for each person
- This product will not work for all men

Stop use and ask a doctor if

- Chest pain, rapid heart beat, faintness, or dissiness occurs
- Sudden, unexplained weight gain occurs
- Your hands of feet swell
- Scalp irritation or redness occurs
- You get unwanted facial hair growth
- You do not see hair regrowth in 4 months

DIRECTIONS

- apply 1mL with sprayer (6 sprays) 2 times a day directly onto the scalp in the hair loss area
- using more or more often will not improve results
- continued use is necessary to increase and keep your hair regrowth, or hair loss will begin again

OTHER SAFETY INFORMATION

- See hair loss pictures on the side of this carton
- Before use, read all information on carton and enclosed leaflet
- Keep the carton. It contains important information
- Hair regrowth has not been shown to last longer than 48 weeks in large clinical trialse with continuous treatment with 5% minoxidil topical solution for men
- In clincial studies of mostly white men aged 18-49 years with moderate degrees of hair loss, 5% minoxidil topical solution for men provide more hair regrowth than 2% minoxidil topical solution
- Store at controlled room temperature 20o to 25o C (68o to 77o F)

INACTIVE INGREDIENT

Alcohol, Propylene Glycol, Purified Water

Keep out of reach of children. If swallowed, get medical help or contact a Poison Control Center right away.

PREGNANCY OR BREAST FEEDING

May be harmful if used when pregnant or breast-feeding.